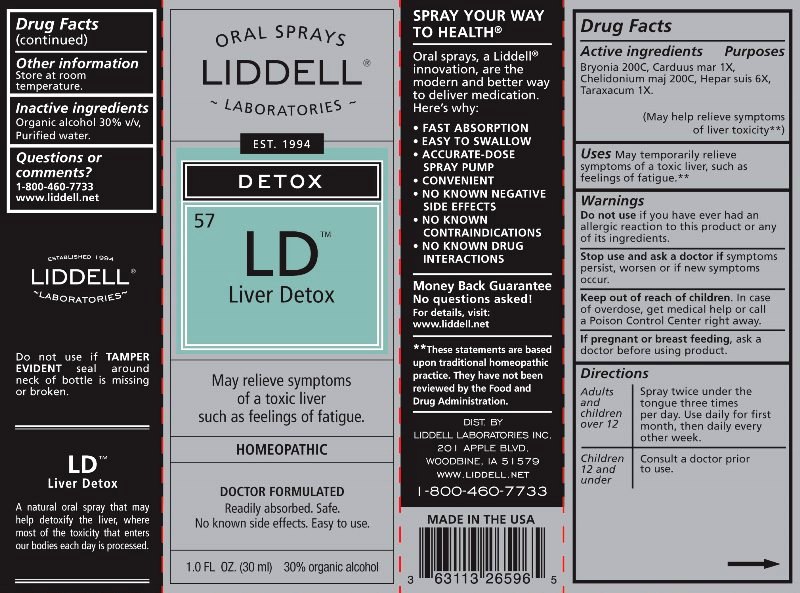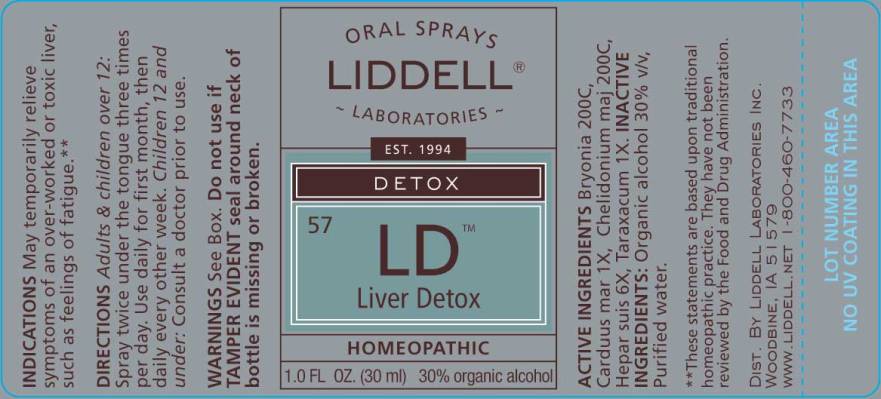 DRUG LABEL: LIVER DETOX
NDC: 50845-0105 | Form: SPRAY
Manufacturer: Liddell Laboratories, Inc.
Category: homeopathic | Type: HUMAN OTC DRUG LABEL
Date: 20240701

ACTIVE INGREDIENTS: BRYONIA ALBA ROOT 200 [hp_C]/1 mL; MILK THISTLE 1 [hp_X]/1 mL; CHELIDONIUM MAJUS WHOLE 200 [hp_C]/1 mL; PORK LIVER 6 [hp_X]/1 mL; TARAXACUM OFFICINALE 1 [hp_X]/1 mL
INACTIVE INGREDIENTS: WATER; ALCOHOL

DRUG FACTS:

ACTIVE INGREDIENTS:

BRYONIA (ALBA) 200C, CARDUUS MARIANUS 1X, CHELIDONIUM MAJUS 200C, HEPAR SUIS 6X, TARAXACUM OFFICINALE 1X

USES:

May temporarily relieve symptoms of a toxic liver, such as feelings of fatigue.**

**These statements are based upon traditional homeopathic practice. They have not been reviewed by the Food and Drug Administration.

WARNINGS:

Do not use if you have ever had an allergic reaction to this product or any of its ingredients.

Stop use and ask a doctor if symptoms persist, worsen or if new symptoms occur.

Keep out of reach of children. In case of overdose, get medical help or call a Poison Control Center.

If pregnant or breast feeding, ask a doctor before using product.

Do not use if TAMPER EVIDENT seal around neck of bottle is missing or broken.

Other information

Store at room temperature.

Keep out of reach of children. In case of overdose, get medical help or call a Poison Control Center.

DIRECTIONS:

Adults and children over 12

Spray twice under the tongue three times per day. Use daily for first month, then daily every other week.

Children 12 and under

Consult a doctor prior to use.

USES:

May temporarily relieve symptoms of a toxic liver, such as feelings of fatigue.**

**These statements are based upon traditional homeopathic practice. They have not been reviewed by the Food and Drug Administration.

INACTIVE INGREDIENTS:

Organic alcohol 30% v/v, Purified water.

QUESTIONS:

DIST. BY

LIDDELL LABORATORIES INC.

201 APPLE BLVD.

WOODBINE, IA 51579

WWW.LIDDELL.NET

1-800-460-7733

PACKAGE LABEL DISPLAY:

ORAL SPRAYS

LIDDELL
LABORATORIES
EST. 1994

DETOX
57

LD
LIVER DETOX

May relieve symptoms
of a toxic liver
such as feelings of fatigue.

HOMEOPATHIC

DOCTOR FORMULATED
Readily absorbed. Safe.
No known side effects. Easy to use.

1.0 FL OZ. (30 ml)